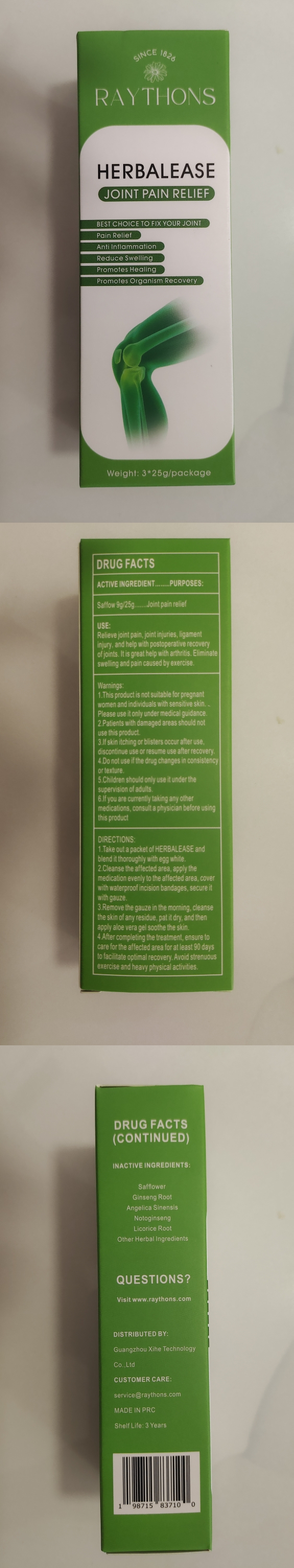 DRUG LABEL: HERBALEASE
NDC: 84672-101 | Form: POWDER
Manufacturer: Guangzhou Xihe Technology Co., Ltd
Category: otc | Type: HUMAN OTC DRUG LABEL
Date: 20241008

ACTIVE INGREDIENTS: SAFFLOWER 9 g/25 g
INACTIVE INGREDIENTS: ANGELICA SINENSIS WHOLE; LICORICE; PANAX NOTOGINSENG ROOT; PANAX NOTOGINSENG WHOLE; ASIAN GINSENG

Active ingredients: safflow 9g/25g

PURPOSE

Relieve joint pain, joint injuries, ligament injury, and help with postoperative recovery of joints. It is great help with arthritis. Eliminate swelling and pain caused by exercise.

INDICATIONS AND USAGE

USE: This product is used to relieve joint pain, joint injuries, ligament injury, and help with postoperative recovery of joints. It is great help with arthritis. Eliminate swelling and pain caused by exercise.

INSTRUCTIONS：Take out a packet of HERBALEASE and blend it thoroughly with egg white.

Cleanse the affected area, apply the medication evenly to the affected area, wrap it with cling film, and secure it with gauze.

Warning:

This product is not suitable for pregnant women and individuals with sensitive skin. Please use it only under medical guidance.

Patients with damaged areas should not use this product.

If skin itching or blisters occur after use, discontinue use or resume use after recovery.

Do not use if the drug changes in consistency or texture.

Children should only use it under the supervision of adults.

If you are currently taking any other medications, consult a physician before using this product

DOSAGE AND ADMINISTRATION

1 pack/day

INACTIVE INGREDIENT

Inactive ingredients: PANAX NOTOGINSENG, GINSENG ROOT, ANGILICA SINENSIS, NOTOGINSENG, LICORICE ROOT

Keep out of reach of children.lf swallowed, get medical help or contact a Poison Control Center.

Label